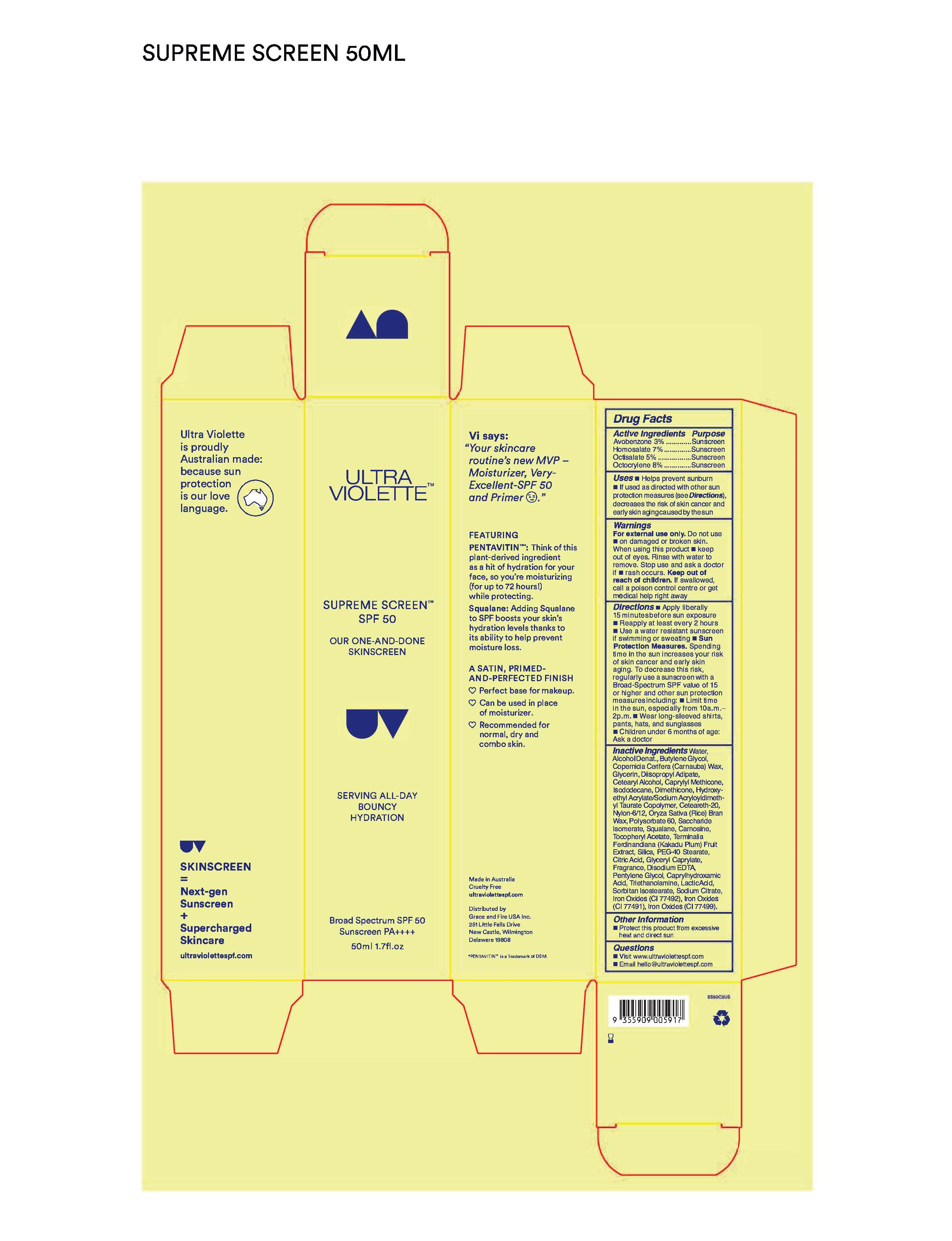 DRUG LABEL: Ultra Violette Supreme Screen Broad Spectrum SPF 50
NDC: 84803-100 | Form: CREAM
Manufacturer: Grace and Fire USA Inc.
Category: otc | Type: HUMAN OTC DRUG LABEL
Date: 20260119

ACTIVE INGREDIENTS: HOMOSALATE 70 mg/1 mL; AVOBENZONE 30 mg/1 mL; OCTISALATE 50 mg/1 mL; OCTOCRYLENE 80 mg/1 mL
INACTIVE INGREDIENTS: DIMETHICONE, UNSPECIFIED; CAPRYLYL TRISILOXANE; CETOSTEARYL ALCOHOL; KAKADU PLUM; .ALPHA.-TOCOPHEROL ACETATE; CITRIC ACID MONOHYDRATE; CAPRYLHYDROXAMIC ACID; SODIUM CITRATE; PENTYLENE GLYCOL; LACTIC ACID; CARNAUBA WAX; WATER; SQUALANE; FERRIC OXIDE YELLOW; SILICON DIOXIDE; GLYCERYL CAPRYLATE; SORBITAN ISOSTEARATE; FERROSOFERRIC OXIDE; DIISOPROPYL ADIPATE; ALCOHOL; BUTYLENE GLYCOL; GLYCERIN; ISODODECANE; RICE BRAN; POLYSORBATE 60; POLYOXYL 20 CETOSTEARYL ETHER; NYLON-12; SACCHARIDE ISOMERATE; EDETATE DISODIUM; CARNOSINE; PEG-40 MONOSTEARATE; HYDROXYETHYL ACRYLATE/SODIUM ACRYLOYLDIMETHYL TAURATE COPOLYMER (100000 MPA.S AT 1.5%); TROLAMINE; FERRIC OXIDE RED

ACTIVE INGREDIENTS

AVOBENZONE 3.0%
HOMOSALATE 7.0%
OCTISALATE 5.0%
OCTOCRYLENE 8.0%

PURPOSE

SUNSCREEN

USE

HELPS PREVENT SUNBURN

if used as directed with other sun protection measures (see Directions), decreases the risk of skin cancer and early skin aging caused by the sun

WARNINGS

Do not use

on damaged or broken skin

When using this product

keep out of eyes. Rinse with water to remove.

Stop use and ask a doctor if

rash occurs

Keep out of reach of children

If swallowed, get medical help or contact a Poison Control Center right away.

Directions

- Apply liberally 15 minutes before sun exposure
- Reapply at least every 2 hours
- Use a water resistant sunscreen if swimming or sweating
- Sun Protection Measures. Spending time in the sun increases your risk of skin cancer and early skin aging. To decrease this risk, regularly use a sunscreen with a Broad Spectrum SPF value of 15 or higher and other sun protection measures including:
- limit time in the sun, especially from 10 a.m. – 2 p.m.
- wear long-sleeved shirts, pants, hats, and sunglasses
- children under 6 months of age: Ask a doctor

Inactive Ingredients

Water, Alcohol Denat., Butylene Glycol, Diisopropyl Adipate, Glycerin, Cetearyl Alcohol, Caprylyl Methicone, lsododecane, Copernicia Cerifera (Camauba) Wax, Oryza Saliva (Rice) Bran Wax, Polysorbate 60, Dimethicone, Ceteareth-20, Nylon- 6/12, Saccharide lsomerate, Squalane, Camosine, Tocopheryl Acetate, Terminalia Ferdinandiana (Kakadu Plum) Fruit Extract, Silica, PEG-40 Stearate, Citric Acid, Hydroxyethyl Acrylate/Sodium Acryloyldimethyl Taurate Copolymer, Glyceryl Caprylate, Fragrance, Disodium EDTA,
Pentylene Glycol, Caprylhydroxamic Acid, Triethanolamine, Lactic Acid, Sorbitan lsostearate, Sodium Citrate, Iron Oxides (Cl 77491), Iron Oxides (Cl 77492), Iron Oxides (Cl 77499).

Other Information

protect this product from excessive heat and direct sun

PRINCIPAL DISPLAY PANEL

Supreme Screen Broad Spectrum SPF 50

1.7 FL. OZ. (50 mL)